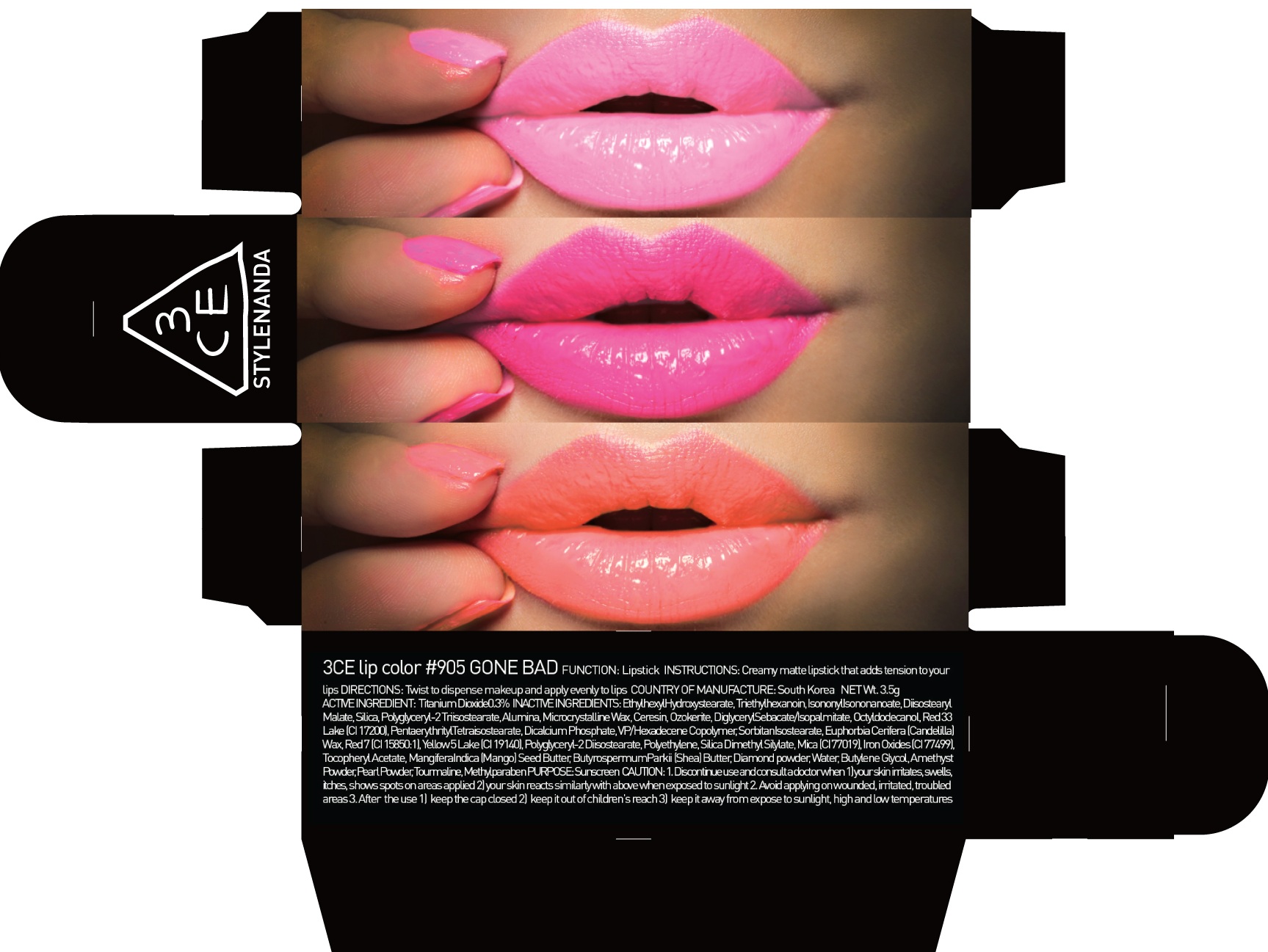 DRUG LABEL: 3CE LIP COLOR 905 GONE BAD
NDC: 60764-049 | Form: LIPSTICK
Manufacturer: Nanda Co., Ltd
Category: otc | Type: HUMAN OTC DRUG LABEL
Date: 20161019

ACTIVE INGREDIENTS: Titanium Dioxide 0.01 g/3.5 g
INACTIVE INGREDIENTS: Ethylhexyl Hydroxystearate; Triethylhexanoin

ACTIVE INGREDIENT

Active Ingredient: Titanium Dioxide 0.3%

INACTIVE INGREDIENT

Inactive Ingredients: Ethylhexyl Hydroxystearate, Triethylhexanoin, IsononylIsononanoate, Diisostearyl Malate, Silica, Polyglyceryl-2 Triisostearate, Alumina, Microcrystalline Wax, Ceresin, Ozokerite, DiglycerylSebacate/Isopalmitate, Octyldodecanol, Red 33 Lake (CI 17200), PentaerythritylTetraisostearate, Dicalcium Phosphate, VP/Hexadecene Copolymer, SorbitanIsostearate, Euphorbia Cerifera (Candelilla) Wax, Red 7 (CI 15850:1), Yellow 5 Lake (CI 19140), Polyglyceryl-2 Diisostearate, Polyethylene, Silica Dimethyl Silylate, Mica (CI 77019), Iron Oxides (CI 77499), Tocopheryl Acetate, MangiferaIndica (Mango) Seed Butter, ButyrospermumParkii (Shea) Butter, Diamond powder, Water, Butylene Glycol, Amethyst Powder, Pearl Powder, Tourmaline, Methylparaben

PURPOSE

Purpose: Sunscreen

CAUTION

CAUTION: 1. Discontinue use and consult a doctor when - your skin irritates, swells, itches, shows spots on areas applied - your skin reacts similarly with above when exposed to sunlight 2. Avoid applying on wounded, irritated, troubled areas 3. After the use - keep the cap closed - keep it out of children's reach - keep it away from expose to sunlight, high and low temperatures

DESCRIPTION

INSTRUCTIONS: A rich color lipstick that moistly adheres to lips.

Directions: Twist to dispense makeup and apply evenly to lips